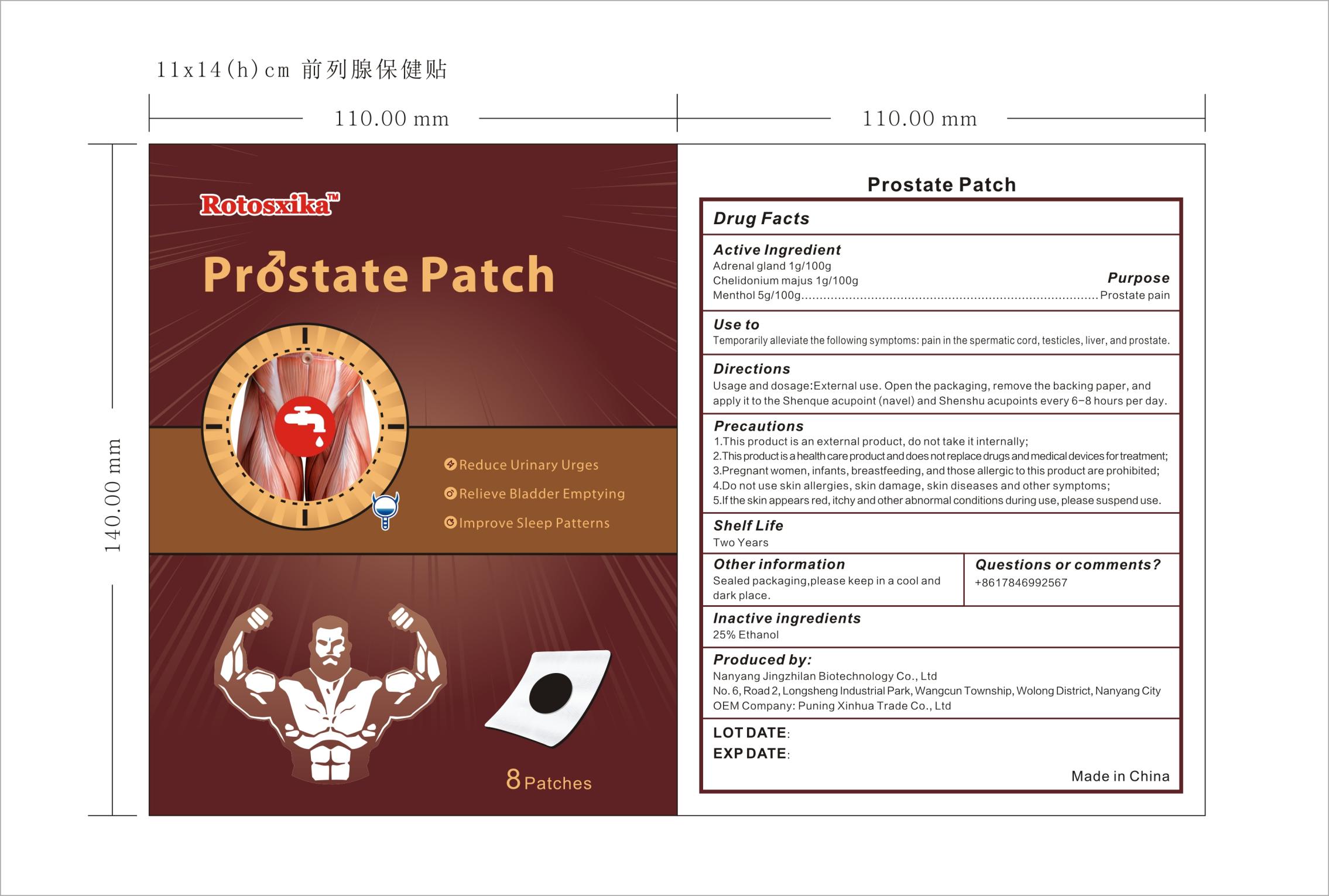 DRUG LABEL: Rotosxika Prostate Patch
NDC: 83702-019 | Form: PATCH
Manufacturer: Puning Xinhua Trade Co., Ltd.
Category: otc | Type: HUMAN OTC DRUG LABEL
Date: 20231018

ACTIVE INGREDIENTS: HUMAN ADRENAL GLAND 1 g/100 g; MENTHOL, UNSPECIFIED FORM 5 g/100 g; CHELIDONIUM MAJUS 1 g/100 g
INACTIVE INGREDIENTS: ALCOHOL

Prostate Patch-83702-019-12

Active Ingredient: Adrenal gland 1g/100g, Chelidonium majus 1g/100g, Menthol 5g/100g

Purpose: Prostate pain

INDICATIONS AND USAGE

Use to:

Temporarily alleviate the following symptoms: pain in the spermatic cord, testicles, liver, and prostate.

Directions
Usage and dosage:External use. Open the packaging, remove the backing paper, and apply it to the Shenque acupoint (navel) and Shenshu acupoints every 6-8 hours per day.

WARNINGS

Precautions
1.This product is an external product, do not take it internally;
2.This product is a health care product and does not replace drugs and medical devices fortreatment;
3.Pregnant women, infants, breastfeeding, and those allergic to this product are prohibited;
4.Do not use skin allergies, skin damage, skin diseases and other symptoms;
5.If the skin appears red, itchy and other abnormal conditions during use, please suspend use.

Questions or comments?

+8617846992567

Inactive ingredients: 25% Ethanol

Other information:

Sealed packaging,please keep in a cool and dark place.

Produced by:

Nanyang Jingzhilan Biotechnology Co., Ltd

No.6,Road2,Longsheng Industrial Park,Wangcun Township, Wolong District, Nanyang City
OEM Company: Puning Xinhua Trade Co., Ltd

Made in China

KEEP OUT OF REACH OF CHILDREN

Same as WARNINGS SECTION

Label